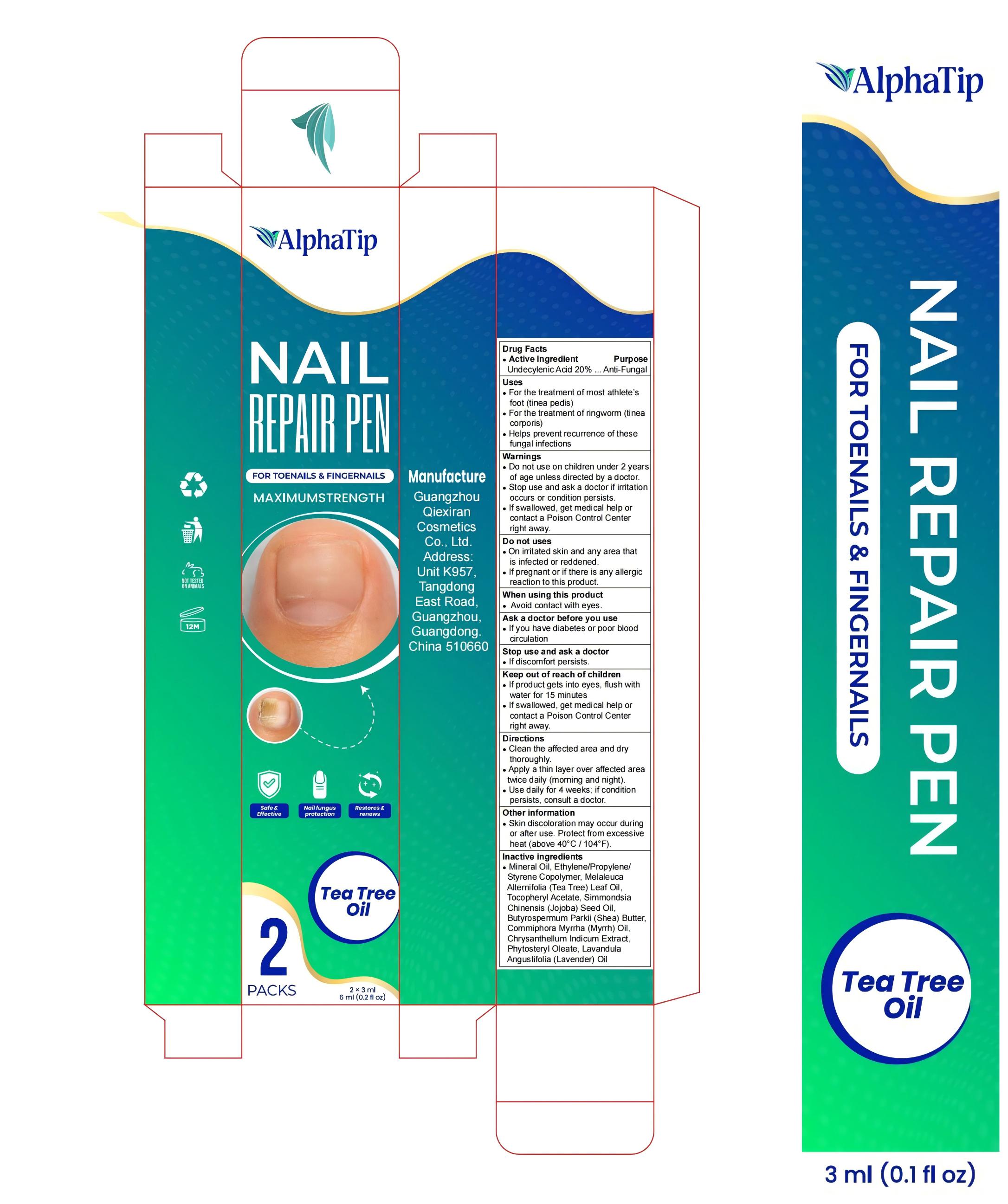 DRUG LABEL: AlphaTip Nail Repair Pen
NDC: 85817-008 | Form: LIQUID
Manufacturer: Guangzhou Qiexiran Cosmetics Co., Ltd.
Category: otc | Type: HUMAN OTC DRUG LABEL
Date: 20251111

ACTIVE INGREDIENTS: UNDECYLENIC ACID 20 g/100 mL
INACTIVE INGREDIENTS: LAVANDULA ANGUSTIFOLIA (LAVENDER) OIL; ETHYLENE; .ALPHA.-TOCOPHEROL ACETATE; DIHYDROPHYTOSTERYL OCTYLDECANOATE; MELALEUCA ALTERNIFOLIA (TEA TREE) LEAF OIL; SIMMONDSIA CHINENSIS (JOJOBA) SEED OIL; MINERAL OIL; BUTYROSPERMUM PARKII (SHEA) BUTTER; COMMIPHORA MYRRHA OIL; CHRYSANTHELLUM INDICUM WHOLE

85817-008

Active Ingredient

Undecylenic Acid 20%

Purpose

Anti-Fungal

Use

For the treatment of most athlete’s foot (tinea pedis)
For the treatment of ringworm (tinea corporis)
Helps prevent recurrence of these fungal infections

Warnings

Do not use on children under 2 years of age unless directed by a doctor.
Stop use and ask a doctor if irritation occurs or condition persists.
If swallowed, get medical help or contact a Poison Control Center right away.

Do not use

On irritated skin and any area that is infected or reddened.
If pregnant or if there is any allergic reaction to this product.

When Using

Avoid contact with eyes.

Stop Use

If you have diabetes or poor blood circulation

Ask Doctor

If discomfort persists.

Keep Out Of Reach Of Children

If product gets into eyes, flush with water for 15 minutes
If swallowed, get medical help or contact a Poison Control Center right away.

Directions

Clean the affected area and dry thoroughly.
Apply a thin layer over affected area twice daily (morning and night).
Use daily for 4 weeks; if condition persists, consult a doctor.

Other information

Skin discoloration may occur during or after use. Protect from excessive heat (above 40°C / 104°F)

Inactive ingredients

Mineral Oil, Ethylene/Propylene/Styrene Copolymer, Melaleuca Alternifolia (Tea Tree) Leaf Oil, Tocopheryl Acetate, Simmondsia Chinensis (Jojoba) Seed Oil, Butyrospermum Parkii (Shea) Butter, Commiphora Myrrha Oil, Chrysanthellum Indicum Extract, Phytosteryl Oleate, Lavandula Angustifolia (Lavender) Oil.